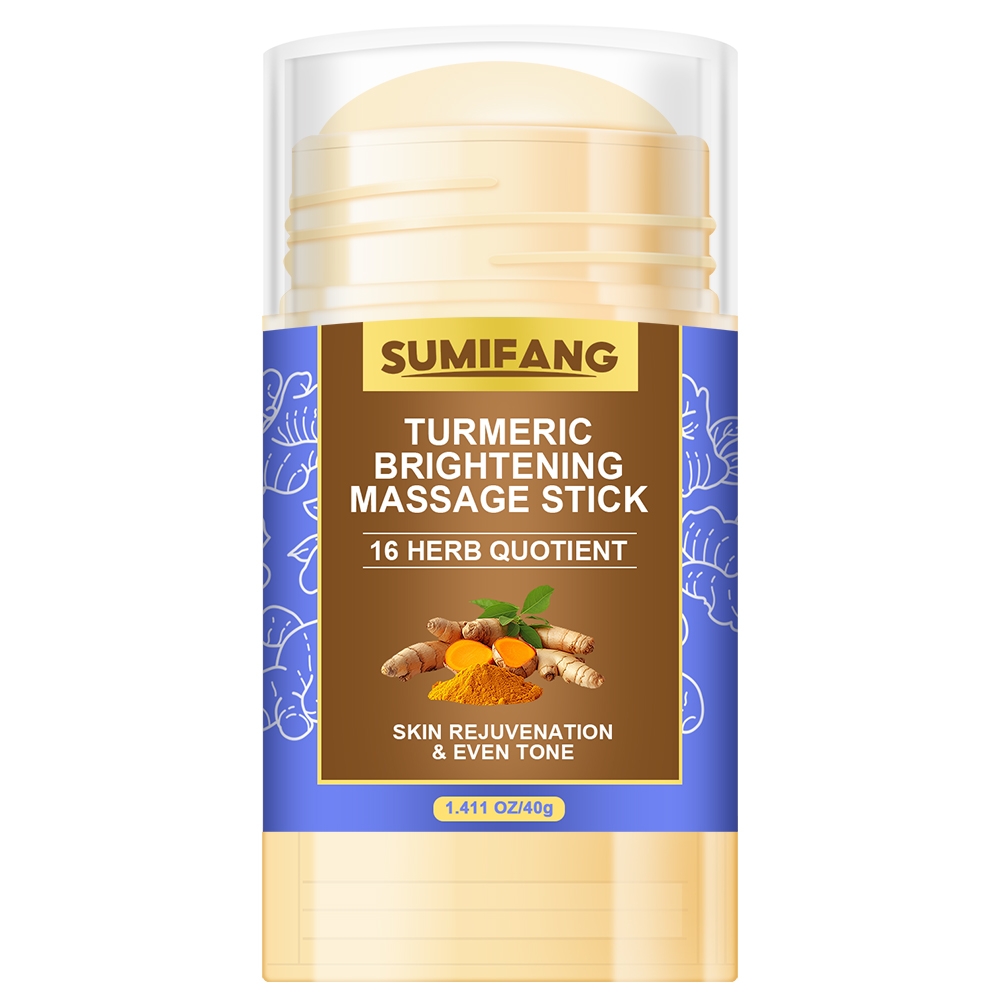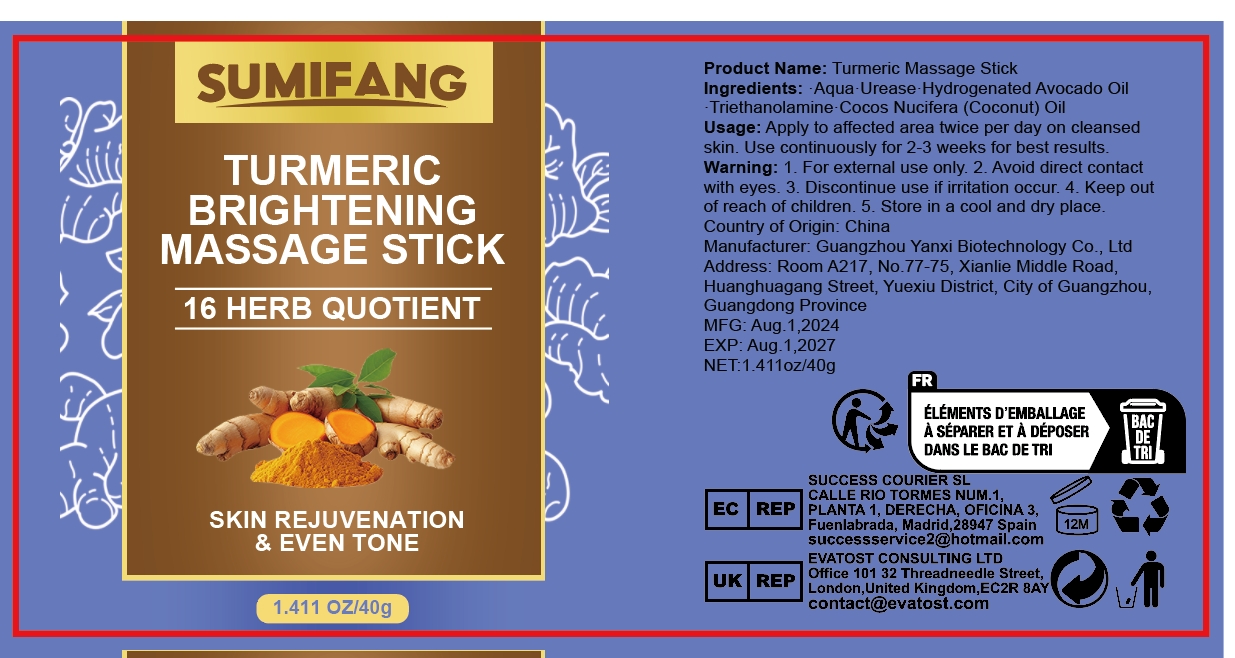 DRUG LABEL: TURMERIC BRIGHTENING MASSAGESTICK
NDC: 84025-115 | Form: STICK
Manufacturer: Guangzhou Yanxi Biotechnology Co.. Ltd
Category: otc | Type: HUMAN OTC DRUG LABEL
Date: 20240805

ACTIVE INGREDIENTS: HYDROGENATED AVOCADO OIL 5 mg/40 g
INACTIVE INGREDIENTS: WATER

DOSAGE AND ADMINISTRATION

stick for moisturizing and massaging the skin

WARNINGS

Keep out of children

INACTIVE INGREDIENT

Aqua

INDICATIONS AND USAGE

For daily skin care

Keep out of children

PURPOSE

Massages the skin and relieves discomfort